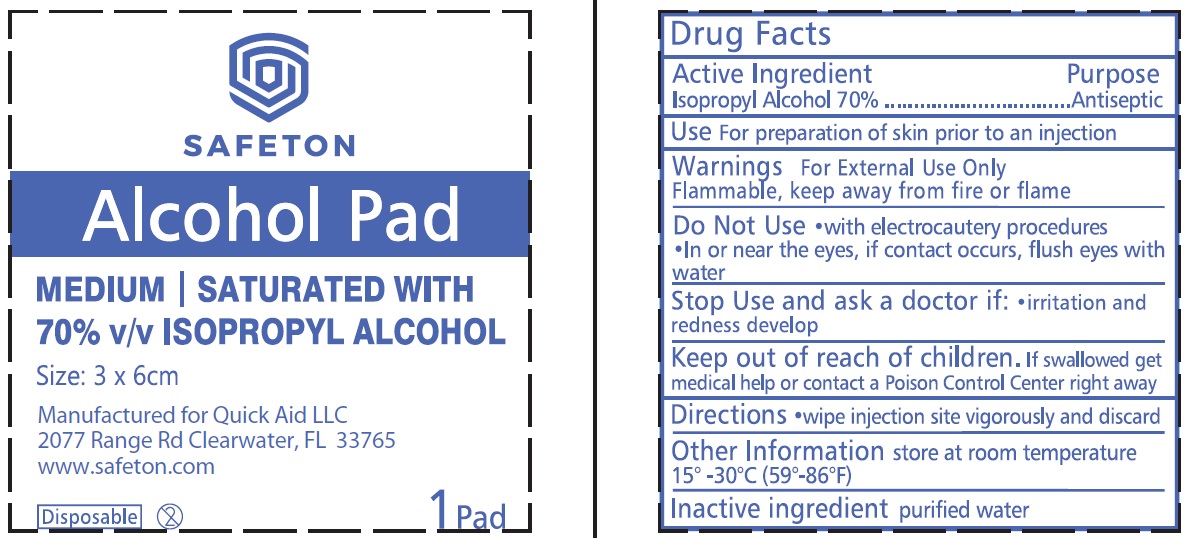 DRUG LABEL: Safeton Alcohol Pad 70 Isopropyl Alcohol
NDC: 83006-003 | Form: SWAB
Manufacturer: QUICK AID LLC
Category: otc | Type: HUMAN OTC DRUG LABEL
Date: 20221019

ACTIVE INGREDIENTS: ISOPROPYL ALCOHOL 0.7 mL/1 g
INACTIVE INGREDIENTS: WATER

Safeton Alcohol Pad 70% Isopropyl Alcohol

Active Ingredient

Isopropyl Alcohol 70%

Purpose

Antiseptic

Use

For preparation of skin prior to an injection

Warnings

For External Use Only

Flammable, keep away from fire or flame

Do Not Use

- with electrocautery procedures
- In or near the eyes, if contact occurs, flush eyes with water

Stop Use and ask a doctor if:

- irritation and redness develop

Keep out of reach of children.

If swallowed get medical help or contact a Poison Control Center right away

Directions

- wipe injection site vigorously and discard

Other Information

store at room temperature 15°-30°C (59°-86°F)

Inactive ingredients

purified water